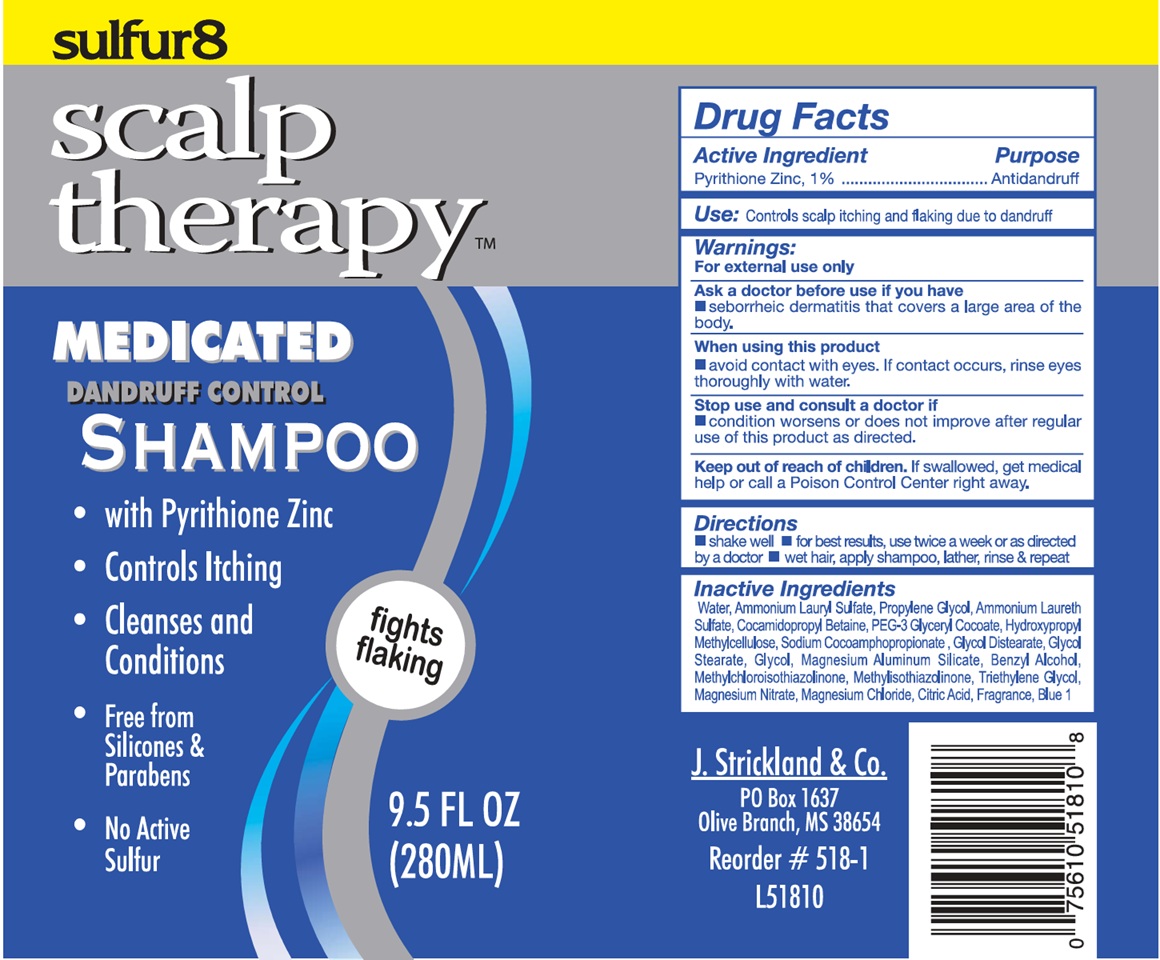 DRUG LABEL: Sulfur 8 Scalp Therapy Medicated Dandruff Control
NDC: 12022-036 | Form: SHAMPOO, SUSPENSION
Manufacturer: J. Strickland and Co.
Category: otc | Type: HUMAN OTC DRUG LABEL
Date: 20251107

ACTIVE INGREDIENTS: PYRITHIONE ZINC 10 mg/1 mL
INACTIVE INGREDIENTS: WATER; AMMONIUM LAURYL SULFATE; PROPYLENE GLYCOL; COCAMIDOPROPYL BETAINE; HYPROMELLOSE, UNSPECIFIED; GLYCOL DISTEARATE; GLYCOL STEARATE; ETHYLENE GLYCOL; MAGNESIUM ALUMINUM SILICATE; BENZYL ALCOHOL; METHYLCHLOROISOTHIAZOLINONE; METHYLISOTHIAZOLINONE; TRIETHYLENE GLYCOL; MAGNESIUM NITRATE; CUPRIC SULFATE; CITRIC ACID MONOHYDRATE; FD&C BLUE NO. 1

Sulfur 8 Scalp Therapy Medicated Dandruff Control Shampoo

Active Ingredient

Pyrithione Zinc, 1%

Purpose

Antidandruff

Use

Controls scalp itching an flaking due to dandruff

Warnings

For external use only

Ask a doctor before use if you have

seborrheic dermatitis that covers a large area of the body.

When using this product

avoid contact with eyes. If contact occurs rinse eyes thoroughly with water.

Stop use and consult a doctor if

- condition worsens or does not improve after regular use of this product as directed.

Keep out of reach of children.

If swallowed, get medical help or call a Poison Control Center right away.

Directions

- shake well.
- for best results, use twice a week or as directed by a doctor
- wet hair, apply shampoo. lather, rinse & repeat

Inactive Ingredients

Water, Ammonium Lauryl Sulfate, Propylene Glycol, Ammonium Laureth Sulfate, Cocamidopropyl Betaine, PEG-3 Glyceryl Cocoate, Hydroxypropyl Methylcellulose, Sodium Cocoamphopropionate, Glycol Distearate, Glycol Stearate, Glycol, Magnesium Aluminum Silicate, Benzyl Alcohol, Methylchloroisothiazolinone, Methylisothiazolinone, Triethylene Glycol, Magnesium Nitrate, Copper Sulfate, Citric Acid, Fragrance, Blue 1